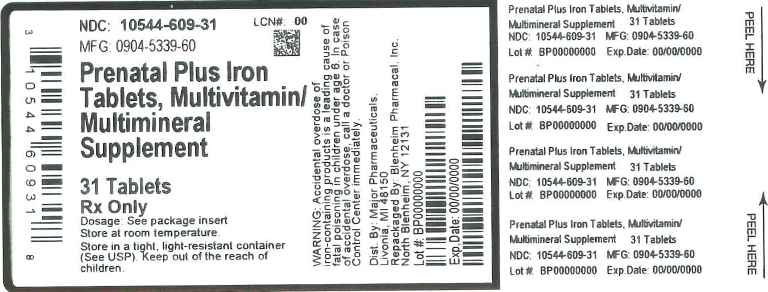 DRUG LABEL: PRENATAL PLUS IRON
NDC: 10544-609 | Form: TABLET, FILM COATED
Manufacturer: Blenheim Pharmacal, Inc.
Category: prescription | Type: HUMAN PRESCRIPTION DRUG LABEL
Date: 20160112

ACTIVE INGREDIENTS: VITAMIN A ACETATE 3080 [iU]/1 1; .BETA.-CAROTENE 920 [iU]/1 1; ASCORBIC ACID 120 mg/1 1; CHOLECALCIFEROL 400 [iU]/1 1; .ALPHA.-TOCOPHEROL ACETATE, DL- 22 [iU]/1 1; THIAMINE MONONITRATE 1.84 mg/1 1; RIBOFLAVIN 3 mg/1 1; NIACINAMIDE 20 mg/1 1; PYRIDOXINE HYDROCHLORIDE 10 mg/1 1; FOLIC ACID 1 mg/1 1; CYANOCOBALAMIN 12 ug/1 1; CALCIUM CARBONATE 200 mg/1 1; IRON PENTACARBONYL 29 mg/1 1; ZINC OXIDE 25 mg/1 1; CUPRIC OXIDE 2 mg/1 1
INACTIVE INGREDIENTS: SILICON DIOXIDE; CROSCARMELLOSE SODIUM; CALCIUM PHOSPHATE, DIBASIC, ANHYDROUS; FD&C BLUE NO. 2; ALUMINUM OXIDE; FD&C RED NO. 40; FD&C YELLOW NO. 5; FD&C YELLOW NO. 6; HYPROMELLOSES; MAGNESIUM STEARATE; CELLULOSE, MICROCRYSTALLINE; STARCH, CORN; PROPYLENE GLYCOL; STEARIC ACID; TITANIUM DIOXIDE; ASCORBYL PALMITATE; ANHYDROUS CITRIC ACID; ETHYLCELLULOSE (100 MPA.S); ANHYDROUS DEXTROSE; ACACIA; MALTODEXTRIN; METHYLCELLULOSE (1500 MPA.S); LIGHT MINERAL OIL; CAPRYLIC/CAPRIC MONO/DIGLYCERIDES; TRICALCIUM PHOSPHATE; METHYL SORBATE; SOY PROTEIN

Prenatal Plus Iron Tablets

DESCRIPTION

Prenatal Plus Iron Tablet is caplet shaped, film coated tablet debossed CIS 28, and provides 10 vitamins and 4 minerals to supplement the diet before, during and after pregnancy.

Each Prenatal Plus tablet Contains:

Vitamin A (Acetate and Beta Carotene)............................................4000 I.U.

Vitamin C (Ascorbic acid)..................................................................120 mg

Vitamin D-3 (Cholecalciferol)...............................................................400 I.U.

Vitamin E (dl- Alpha Tocopheryl Acetate)...........................................22 I.U.

Thiamine (Vitamin B-1 from Thiamine Mononitrate...............................1.84 mg

Riboflavin (Vitamin B-2).......................................................................3 mg

Niacin(Niacinamide).............................................................................20 mg

Vitamin B-6 (Pyridoxine HCl)...............................................................10 mg

Folic Acid.............................................................................................1 mg

Vitamin B-12 (Cyanocobalamin)..........................................................12 mcg

Calcium (Calcium Carbonate)...............................................................200 mg

Iron (Carbonyl Iron)..............................................................................29 mg

Zinc (Zinc Oxide).................................................................................25 mg

Copper (Cupric Oxide)..........................................................................2 mg

Other ingredients: Ascorbyl Palmitate, Citric Acid anhydrous, DL-alpha Tocopherol, Ethylcellulose, FD&C Blue #2 lake, FD&C Red #40 lake, FD&C Yellow # 5 lake, FD&C Yello # 6 lake, Glucose, Gum Acacia, Hypromellose, Magnesium Stearate, Maize Starch, Maltodextrin, Methylcellulose, Microcrystalline Cellulose, Mineral Oil, Mono-and di-glycerides, Polyethyelene Glycol, Pregelatinized Corn Starch, Silicon Dioxide, Sorbic Acid, Soy Protein, Stearic Acid, Sucrose, Titanium Dioxide, Tricalcium Phosphate

INDICATIONS

To provide Vitamin and Mineral supplementation throughout pregnancy and during the postnatal period for both the lactating and non lactating mother. It is also useful for improving nutritional status prior to conception

DOSAGE

As a dietary adjunct before, during and after pregnancy, take one tablet daily with a meal, or as directed by a physician.

WARNING

Warning: Accidental overdose of iron containing products is a leading cause of fatal poisoning in children under age 6. Keep this product out of the reach of children. In case of accidental overdose, call a doctor or poison control center immediately.

Precautions: Folic acid may partially correct the hematological damage due to Vitamin B12 deficiency of pernicious anemia, while the associated neurological damage progesses.

This product contains FD&C Yellow No. 5 (tartrazine) which may cause allergic-type reactions (including bronchial asthma) in certain susceptible persons. Although the overall incidence of FD&C Yello No. 5 (tartrazine) sensitivity in the general population is low, it is frequently seen in patients who also have aspirin hypersensitivity.

STORAGE

Store at room temperature. Dispense in a well closed light resistant container with a child resistant cap.

HOW SUPPLIED

NDC 0904-5339-60 plastic bottle containing 100 Tablets.

Principal Display Panel

Prenatal Plus Iron Tablets (Multivitamin/Multimineral Supplement)
31 Tabets
10544-609-31